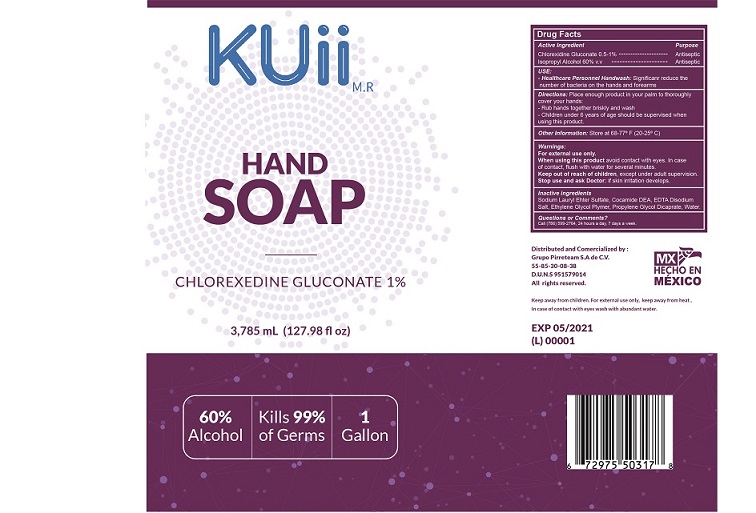 DRUG LABEL: Hand Sanitizer
NDC: 78797-011 | Form: LIQUID
Manufacturer: GRUPO PIRRETEAM SA DE CV
Category: otc | Type: HUMAN OTC DRUG LABEL
Date: 20200831

ACTIVE INGREDIENTS: ISOPROPYL ALCOHOL 60 mg/1 mL; CHLORHEXIDINE GLUCONATE 1 mg/1 mL
INACTIVE INGREDIENTS: EDETATE SODIUM; POLIDOCANOL; PROPYLENE GLYCOL DICAPRATE; COCO DIETHANOLAMIDE; WATER; SODIUM LAURETH SULFATE

Hand Soap Chlorexidine Gluconate

Uses

* Healthcare personnel Handwash. Significant reduce the amount of bacterias on the hands and forearms.

Active Ingredient

Active Ingredient Purpose

- Isopropyl Alcohol 60%...................................Antiseptic
- Chlorhexidine gluconate 0.5%..........................Antiseptic

Warnings

- For external use only
- When using this product avoid contact with eyes. In case of contact, flush with water for several minutes.
- Keep out of reach of children. If swallowed, get medical help, or contact a Poison Control Center right away.
- Stop use and ask Doctor: if skin irritation develops when using this product
- Flammable: Keep away from heat and flame. Highly flammable liquid and vapor/

Stop use and ask a doctor if

* Irritation develops while using this product

Keep out of reach of children. If swallowed, get medical help, or contact a Poison Control Center right away.

Directions

Directions: Place enough product in your palm to throughly cover your hands.

- Rubs hands together briskly until dry
- Children under 6 years of age should be supervised when using this product

Inactive Ingredients

sodium lauryl ether sulfate, cocamide DEA, EDTA disodium salt, ethylene glycol polymer, propylene glycol dicaprate, water

Questions?

QUESTIONS OR COMMENTS: Phone: (786) 599-2764. 24 hours a day, 7 days a week

Uses

* Healthcare personnel Handwash. Significant reduce the amount of bacterias on the hands and forearms.